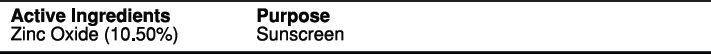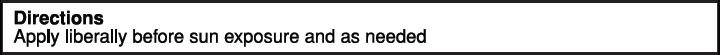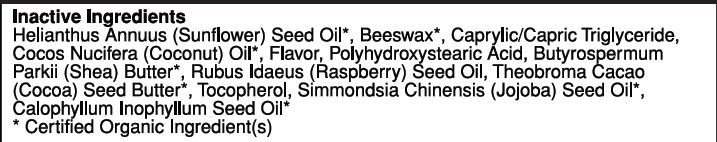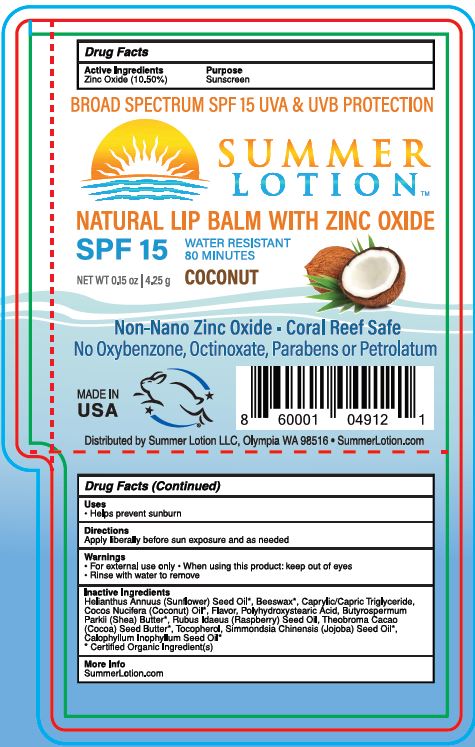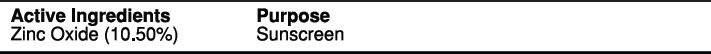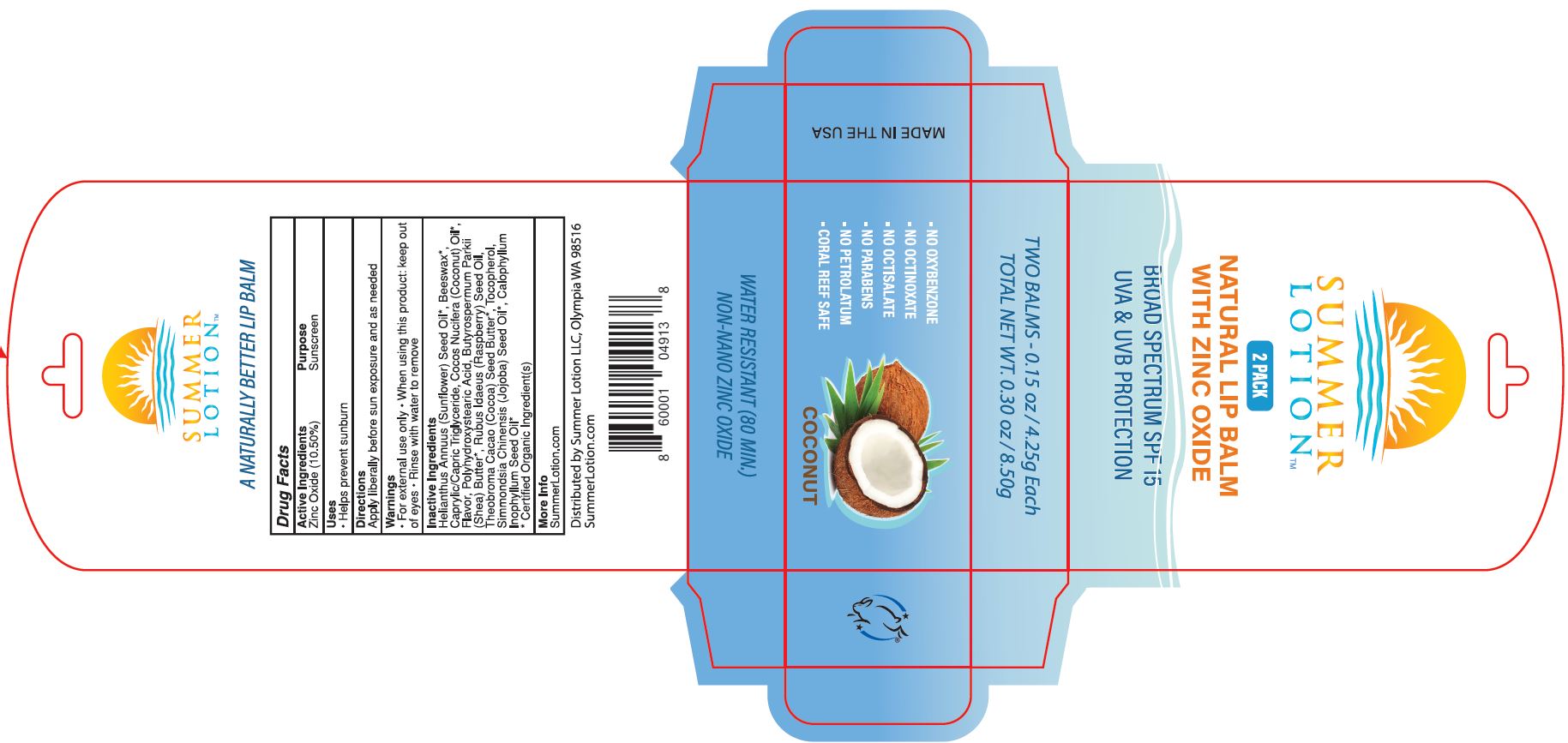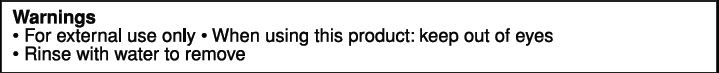 DRUG LABEL: LIP BALM
NDC: 62932-203 | Form: STICK
Manufacturer: Private Label Select Ltd CO
Category: otc | Type: HUMAN OTC DRUG LABEL
Date: 20191227

ACTIVE INGREDIENTS: ZINC OXIDE 15.45 g/100 g
INACTIVE INGREDIENTS: SUNFLOWER OIL; YELLOW WAX; COCONUT OIL; SHEA BUTTER; CAPRYLIC/CAPRIC/LINOLEIC TRIGLYCERIDE; JOJOBA OIL; TAMANU OIL; RASPBERRY SEED OIL; TOCOPHEROL; COCOA BUTTER

Summer Lotion Natural SPF 15 Lip Balm with Zinc Oxide, Coconut